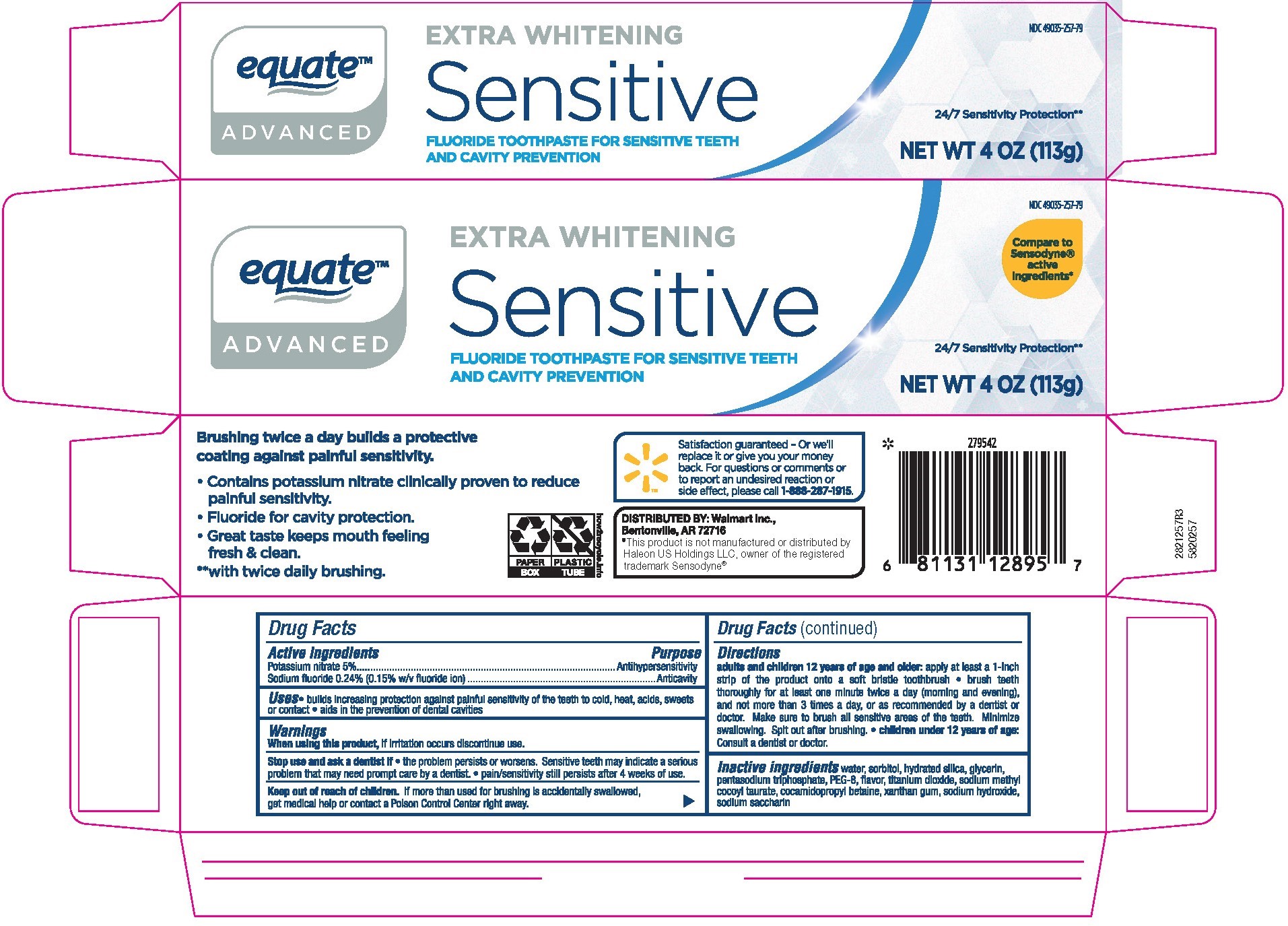 DRUG LABEL: equate Sensitive
NDC: 49035-257 | Form: PASTE, DENTIFRICE
Manufacturer: Wal-Mart Stores Inc
Category: otc | Type: HUMAN OTC DRUG LABEL
Date: 20250808

ACTIVE INGREDIENTS: POTASSIUM NITRATE 5 g/100 g; SODIUM FLUORIDE 0.15 g/100 g
INACTIVE INGREDIENTS: GLYCERIN; SODIUM METHYL COCOYL TAURATE; SACCHARIN SODIUM; XANTHAN GUM; SODIUM HYDROXIDE; HYDRATED SILICA; SODIUM TRIPOLYPHOSPHATE; SORBITOL; TITANIUM DIOXIDE; WATER; COCAMIDOPROPYL BETAINE; POLYETHYLENE GLYCOL 400

5820257 Equate Sensitive Toothpaste with Fluoride

Active ingredients

Potassium nitrate 5%

Sodium fluoride 0.24% (0.15% w/v fluoride ion)

Purpose

Antihypersensitivity

Anticavity

Uses

- builds increasing protection against painful sensitivity of the teeth to cold, heat, acids, sweets or contact
- aids in the prevention of dental cavities

Warnings

When using this product do not use longer than 4 weeks unless recommended by a dentist or physician. See your dentist if the problem persists or worsens. Sensitive teeth may indicate a serious problem that may need prompt care by a dentist.

Keep out of reach of children. If more than used for brushing is accidentally swallowed, get medical help or contact a Poison Control Center right away.

Directions

Adults and children 12 years of age and older: Apply at least a 1-inch strip of the product onto a soft britsle toothbrush. · Brush teeth thoroughly for at least one minute, preferably after each meal or at least twice a day (morning and evening) or as recommended by a dentist or physician. Make sure to brush all sensitive areas of the teeth. Minimize swallowing. Spit out after brushing.

Children under 12 years of age: Consult a dentist or physician.

INACTIVE INGREDIENT

water, sorbitol, hydrated silica, glycerin, pentasodium triphosphate, PEG-8, flavor, titanium dioxide, sodium methyl cocoyltaurate, cocamidopropyl betaine, xanthan gum, sodium hydroxide, sodium saccharin